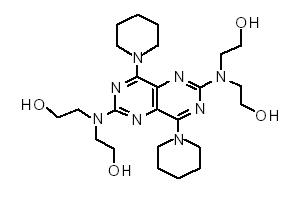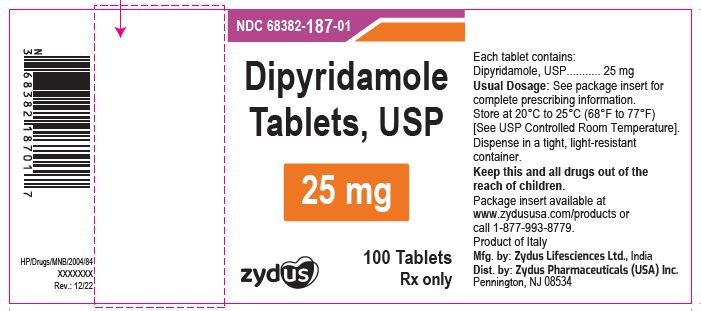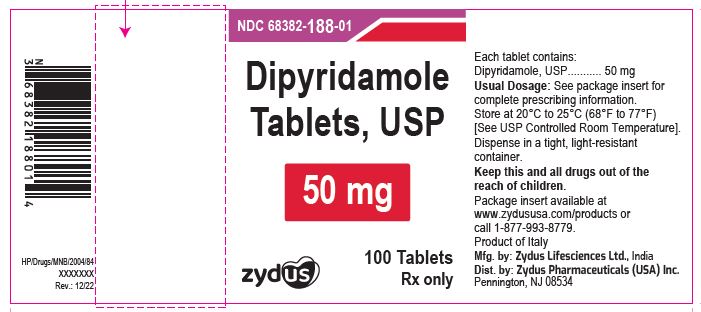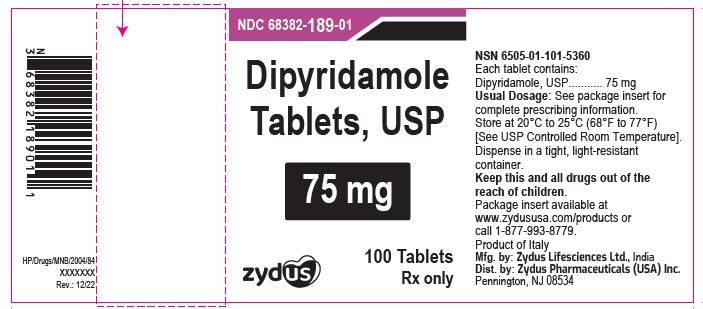 DRUG LABEL: Dipyridamole
NDC: 68382-187 | Form: TABLET, FILM COATED
Manufacturer: Zydus Pharmaceuticals USA Inc.
Category: prescription | Type: HUMAN PRESCRIPTION DRUG LABEL
Date: 20230916

ACTIVE INGREDIENTS: DIPYRIDAMOLE 25 mg/1 1
INACTIVE INGREDIENTS: FERRIC OXIDE YELLOW; HYPROMELLOSE 2910 (6 MPA.S); LACTOSE MONOHYDRATE; MAGNESIUM STEARATE; POLYETHYLENE GLYCOL 3350; POVIDONE K30; TITANIUM DIOXIDE; STARCH, CORN

Dipyridamole Tablets, USP

DESCRIPTION

Dipyridamole is a platelet inhibitor chemically described as 2,2',2'',2'''-[(4,8-Dipiperidinopyrimido[5,4-d]pyrimidine-2,6-diyl)dinitrilo]-tetraethanol. It has the following structural formula:

C24H40N8O4 Mol. Wt. 504.63

Dipyridamole, USP is intensely yellow crystalline powder or needles. It is very soluble in methanol, in alcohol, and in chloroform; slightly soluble in water; very slightly soluble in acetone and in ethyl acetate.

Each dipyridamole tablet intended for oral administration contains 25 mg or 50 mg or 75 mg of dipyridamole. In addition, each tablet contains the following inactive ingredients: corn starch, hypromellose, iron oxide yellow, lactose monohydrate, magnesium stearate, polyethylene glycol, povidone and titanium dioxide.

CLINICAL PHARMACOLOGY

It is believed that platelet reactivity and interaction with prosthetic cardiac valve surfaces, resulting in abnormally shortened platelet survival time, is a significant factor in thromboembolic complications occurring in connection with prosthetic heart valve replacement.

Dipyridamole tablets have been found to lengthen abnormally shortened platelet survival time in a dose-dependent manner.

In three randomized controlled clinical trials involving 854 patients who had undergone surgical placement of a prosthetic heart valve, dipyridamole tablets, in combination with warfarin, decreased the incidence of postoperative thromboembolic events by 62 to 91% compared to warfarin treatment alone. The incidence of thromboembolic events in patients receiving the combination of dipyridamole tablets and warfarin ranged from 1.2 to 1.8%. In three additional studies involving 392 patients taking dipyridamole tablets and coumarin-like anticoagulants, the incidence of thromboembolic events ranged from 2.3 to 6.9%.

In these trials, the coumarin anticoagulant was begun between 24 hours and 4 days postoperatively, and the dipyridamole tablets were begun between 24 hours and 10 days postoperatively. The length of follow-up in these trials varied from 1 to 2 years.

Dipyridamole tablets do not influence prothrombin time or activity measurements when administered with warfarin.

Mechanism of Action

Dipyridamole inhibits the uptake of adenosine into platelets, endothelial cells and erythrocytes in vitro and in vivo; the inhibition occurs in a dose-dependent manner at therapeutic concentrations (0.5 to 1.9 mcg/mL). This inhibition results in an increase in local concentrations of adenosine which acts on the platelet A2-receptor thereby stimulating platelet adenylate cyclase and increasing platelet cyclic-3',5'-adenosine monophosphate (cAMP) levels. Via this mechanism, platelet aggregation is inhibited in response to various stimuli such as platelet activating factor (PAF), collagen and adenosine diphosphate (ADP).

Dipyridamole inhibits phosphodiesterase (PDE) in various tissues. While the inhibition of cAMP-PDE is weak, therapeutic levels of dipyridamole inhibit cyclic-3',5'-guanosine monophosphate-PDE (cGMP-PDE), thereby augmenting the increase in cGMP produced by EDRF (endothelium-derived relaxing factor, now identified as nitric oxide).

Hemodynamics

In dogs intraduodenal doses of dipyridamole of 0.5 to 4.0 mg/kg produced dose-related decreases in systemic and coronary vascular resistance leading to decreases in systemic blood pressure and increases in coronary blood flow. Onset of action was in about 24 minutes and effects persisted for about 3 hours.

Similar effects were observed following intravenous dipyridamole in doses ranging from 0.025 to 2.0 mg/kg.

In man the same qualitative hemodynamic effects have been observed. However, acute intravenous administration of dipyridamole may worsen regional myocardial perfusion distal to partial occlusion of coronary arteries.

Pharmacokinetics and Metabolism

Following an oral dose of dipyridamole tablets, the average time to peak concentration is about 75 minutes. The decline in plasma concentration following a dose of dipyridamole tablets fits a two-compartment model. The alpha half-life (the initial decline following peak concentration) is approximately 40 minutes. The beta half-life (the terminal decline in plasma concentration) is approximately 10 hours. Dipyridamole is highly bound to plasma proteins. It is metabolized in the liver where it is conjugated as a glucuronide and excreted with the bile.

INDICATIONS AND USAGE

Dipyridamole tablets are indicated as an adjunct to coumarin anticoagulants in the prevention of postoperative thromboembolic complications of cardiac valve replacement.

CONTRAINDICATIONS

Hypersensitivity to dipyridamole and any of the other components.

PRECAUTIONS

General

Coronary Artery Disease

Dipyridamole has a vasodilatory effect and should be used with caution in patients with severe coronary artery disease (e.g., unstable angina or recently sustained myocardial infarction). Chest pain may be aggravated in patients with underlying coronary artery disease who are receiving dipyridamole.

Hepatic Insufficiency

Elevations of hepatic enzymes and hepatic failure have been reported in association with dipyridamole administration.

Hypotension

Dipyridamole should be used with caution in patients with hypotension since it can produce peripheral vasodilation.

Stress Testing with Intravenous Dipyridamole and Other Adenosinergic Agents

Clinical experience suggests that patients being treated with dipyridamole tablets who also require pharmacological stress testing with intravenous dipyridamole or other adenosinergic agents (e.g. adenosine, regadenoson) should interrupt dipyridamole tablets for 48 hours prior to stress testing.

Intake of dipyridamole tablets within 48 hours prior to stress testing with intravenous dipyridamole or other adenosinergic agents may increase the risk for cardiovascular side effects of these agents and may impair the sensitivity of the test.

Laboratory Tests

Dipyridamole has been associated with elevated hepatic enzymes.

Drug Interactions

No pharmacokinetic drug-drug interaction studies were conducted with dipyridamole tablets. The following information was obtained from the literature.

Adenosinergic agents (e.g., adenosine, regadenoson)

Dipyridamole has been reported to increase the plasma levels and cardiovascular effects of adenosine. Adjustment of adenosine dosage may be necessary. Dipyridamole also increases the cardiovascular effects of regadenoson, an adenosine A2A-receptor agonist. The potential risk of cardiovascular side effects with intravenous adenosinergic agents may be increased during the testing period when dipyridamole is not held 48 hours prior to stress testing.

Cholinesterase Inhibitors

Dipyridamole may counteract the anticholinesterase effect of cholinesterase inhibitors, thereby potentially aggravating myasthenia gravis.

Carcinogenesis, Mutagenesis, Impairment of Fertility

In studies in which dipyridamole was administered in the feed to mice (up to 111 weeks in males and females) and rats (up to 128 weeks in males and up to 142 weeks in females), there was no evidence of drug-related carcinogenesis. The highest dose administered in these studies (75 mg/kg/day) was, on a mg/m^2 basis, about equivalent to the maximum recommended daily human oral dose (MRHD) in mice and about twice the MRHD in rats. Mutagenicity tests of dipyridamole with bacterial and mammalian cell systems were negative. There was no evidence of impaired fertility when dipyridamole was administered to male and female rats at oral doses up to 500 mg/kg/day (about 12 times the MRHD on a mg/m^2 basis). A significant reduction in number of corpora lutea with consequent reduction in implantations and live fetuses was, however, observed at 1250 mg/kg (more than 30 times the MRHD on a mg/m^2 basis).

Pregnancy

Teratogenic Effects: PREGNANCY CATEGORY B

Reproduction studies have been performed in mice, rabbits and rats at oral dipyridamole doses of up to 125 mg/kg, 40 mg/kg and 1000 mg/kg, respectively (about 11/2, 2 and 25 times the maximum recommended daily human oral dose, respectively, on a mg/m^2 basis) and have revealed no evidence of harm to the fetus due to dipyridamole. There are, however, no adequate and well-controlled studies in pregnant women. Because animal reproduction studies are not always predictive of human response, dipyridamole tablets should be used during pregnancy only if clearly needed.

Nursing Mothers

As dipyridamole is excreted in human milk, caution should be exercised when dipyridamole tablets are administered to a nursing woman.

Pediatric Use

Safety and effectiveness in the pediatric population below the age of 12 years have not been established.

ADVERSE REACTIONS

Adverse reactions at therapeutic doses are usually minimal and transient. On long-term use of dipyridamole tablets initial side effects usually disappear. The following reactions in Table 1 were reported in two heart valve replacement trials comparing dipyridamole tablets and warfarin therapy to either warfarin alone or warfarin and placebo:

Table 1 Adverse Reactions Reported in 2 Heart Valve Replacement Trials
Adverse Reaction | Dipyridamole Tablets/ | Placebo/
 | Warfarin | Warfarin
Number of patients | 147 | 170
Dizziness | 13.6% | 8.2%
Abdominal distress | 6. 1% | 3.5%
Headache | 2.3% | 0.0%
Rash | 2.3% | 1.1%

Other reactions from uncontrolled studies include diarrhea, vomiting, flushing and pruritus. In addition, angina pectoris has been reported rarely and there have been rare reports of liver dysfunction. On those uncommon occasions when adverse reactions have been persistent or intolerable, they have ceased on withdrawal of the medication.

When dipyridamole tablets were administered concomitantly with warfarin, bleeding was no greater in frequency or severity than that observed when warfarin was administered alone. In rare cases, increased bleeding during or after surgery has been observed.

In post-marketing reporting experience, there have been rare reports of hypersensitivity reactions (such as rash, urticaria, severe bronchospasm, and angioedema), larynx edema, fatigue, malaise, myalgia, arthritis, nausea, dyspepsia, paresthesia, hepatitis, thrombocytopenia, alopecia, cholelithiasis, hypotension, palpitation, and tachycardia.

OVERDOSAGE

In case of real or suspected overdose, seek medical attention or contact a Poison Control Center immediately. Careful medical management is essential. Based upon the known hemodynamic effects of dipyridamole, symptoms such as warm feeling, flushes, sweating, restlessness, feeling of weakness and dizziness may occur. A drop in blood pressure and tachycardia might also be observed.

Symptomatic treatment is recommended, possibly including a vasopressor drug. Gastric lavage should be considered. Administration of xanthine derivatives (e.g., aminophylline) may reverse the hemodynamic effects of dipyridamole overdose. Since dipyridamole is highly protein bound, dialysis is not likely to be of benefit.

DOSAGE AND ADMINISTRATION

Adjunctive Use in Prophylaxis of Thromboembolism after Cardiac Valve Replacement

The recommended dose is 75 to 100 mg four times daily as an adjunct to the usual warfarin therapy. Please note that aspirin is not to be administered concomitantly with coumarin anticoagulants.

HOW SUPPLIED

Dipyridamole Tablets USP, 25 mg are light yellow, round, biconvex, film-coated tablets debossed with 'ZE 43' on one side and plain on the other side are supplied as follows:

NDC 68382-187-01 in bottle of 100 tablets

NDC 68382-187-05 in bottle of 500 tablets

NDC 68382-187-10 in bottle of 1000 tablets

NDC 68382-187-77 in unit-dose blister cartons of 100 (10 x 10) unit-dose tablets

Dipyridamole Tablets USP, 50 mg are light yellow, round, biconvex, beveled-edge, film-coated tablets debossed with 'ZE 49' on one side and plain on the other side are supplied as follows:

NDC 68382-188-01 in bottle of 100 tablets

NDC 68382-188-05 in bottle of 500 tablets

NDC 68382-188-10 in bottle of 1000 tablets

NDC 68382-188-77 in unit-dose blister cartons of 100 (10 x 10) unit-dose tablets

Dipyridamole Tablets USP, 75 mg are light yellow, round, biconvex, beveled-edge, film-coated tablets debossed with 'ZE 50' on one side and plain on the other side are supplied as follows:

NDC 68382-189-01 in bottle of 100 tablets

NDC 68382-189-05 in bottle of 500 tablets

NDC 68382-189-10 in bottle of 1000 tablets

NDC 68382-189-77 in unit-dose blister cartons of 100 (10 x 10) unit-dose tablets

STORAGE

Store at 20°C to 25°C (68°F to 77°F) [See USP Controlled Room Temperature]. Keep out of reach of children.

Dispense in a tight, light-resistant container.

Package insert available at www.zydususa.com/products or call 1-877-993-8779.

Manufactured by:

Zydus Lifesciences Ltd.

Ahmedabad, India

Distributed by:

Zydus Pharmaceuticals (USA) Inc.

Pennington, NJ 08534

Rev.: 12/22

PACKAGE LABEL.PRINCIPAL DISPLAY PANEL

NDC 68382-187-05 in bottle of 500 tablets

Dipyridamole Tablets USP, 25 mg

Rx only

500 tablets

NDC 68382-188-05 in bottle of 500 tablets

Dipyridamole Tablets USP, 50 mg

Rx only

500 tablets

NDC 68382-189-05 in bottle of 500 tablets

Dipyridamole Tablets USP, 75 mg

Rx only

500 tablets